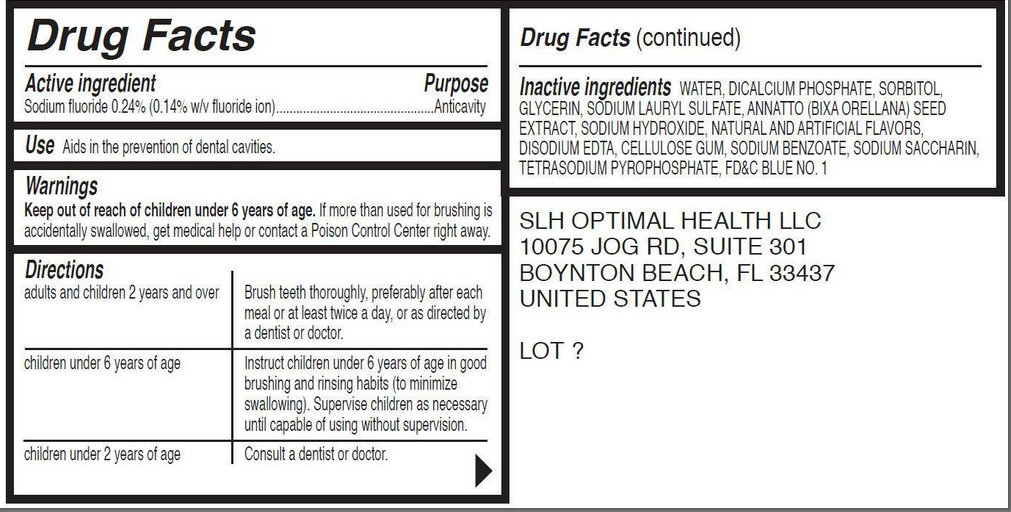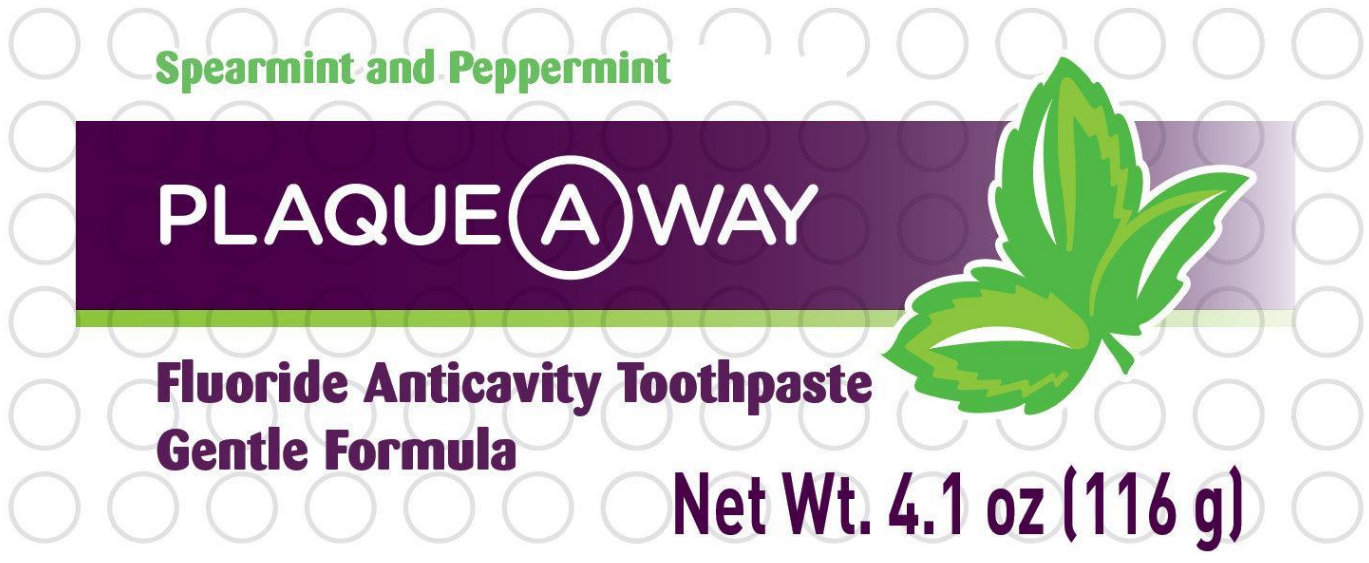 DRUG LABEL: Spearmint and Peppermint PLAQUE A WAY Fluoride AnticavityGentle Formula
  
NDC: 42288-000 | Form: PASTE, DENTIFRICE
Manufacturer: SLH Optimal Health LLC
Category: otc | Type: HUMAN OTC DRUG LABEL
Date: 20121004

ACTIVE INGREDIENTS: SODIUM FLUORIDE 0.24 g/100 g
INACTIVE INGREDIENTS: WATER; CALCIUM PHOSPHATE, DIBASIC, ANHYDROUS; SORBITOL; GLYCERIN; SODIUM LAURYL SULFATE; BIXA ORELLANA SEED; SODIUM HYDROXIDE; EDETATE DISODIUM; CARBOXYMETHYLCELLULOSE SODIUM; SODIUM BENZOATE; SACCHARIN SODIUM DIHYDRATE; SODIUM PYROPHOSPHATE; FD&C BLUE NO. 1

Spearmint and Peppermint PLAQUE A WAY Fluoride Anticavity Toothpaste Gentle Formula

Active Ingredient

Sodium fluoride 0.24% (0.14 w/v fluoride ion)

Purpose

Anticavity

Use

Aids in the prevention of dental cavities.

Warnings

Keep out of reach of children under 6 years of age. If more than used for brushing is accidentally swallowed, get medical help or contact a Poison Control Center right away.

Directions

adults and children 2 years and over | Brush teeth thoroughly, preferably after each meal or at least twice a day, or as directed by a dentist or doctor.
children under 6 years of age | Instruct children under 6 years of age in good brushing and rinsing habits (to minimize swallowing). Supervise children as necessary until capable of using without a supervision.
children under 2 years of age | Consult a dentist or doctor.

Inactive Ingredients

WATER, DICALCIUM PHOSHATE, SORBITOL, GLYCERIN, SODIUM LAURYL SULFATE, ANNATTO (BIXA ORELLANA) SEED EXTRACT, SODIUM HYDROXIDE, NATURAL AND ARTIFICIAL FLAVORS, DISODIUMM EDTA, CELLULOSE GUM, SODIUM SACCHARIN, TETRASODIUM PYROPHOSPHATE, FD AND C BLUE NO.1